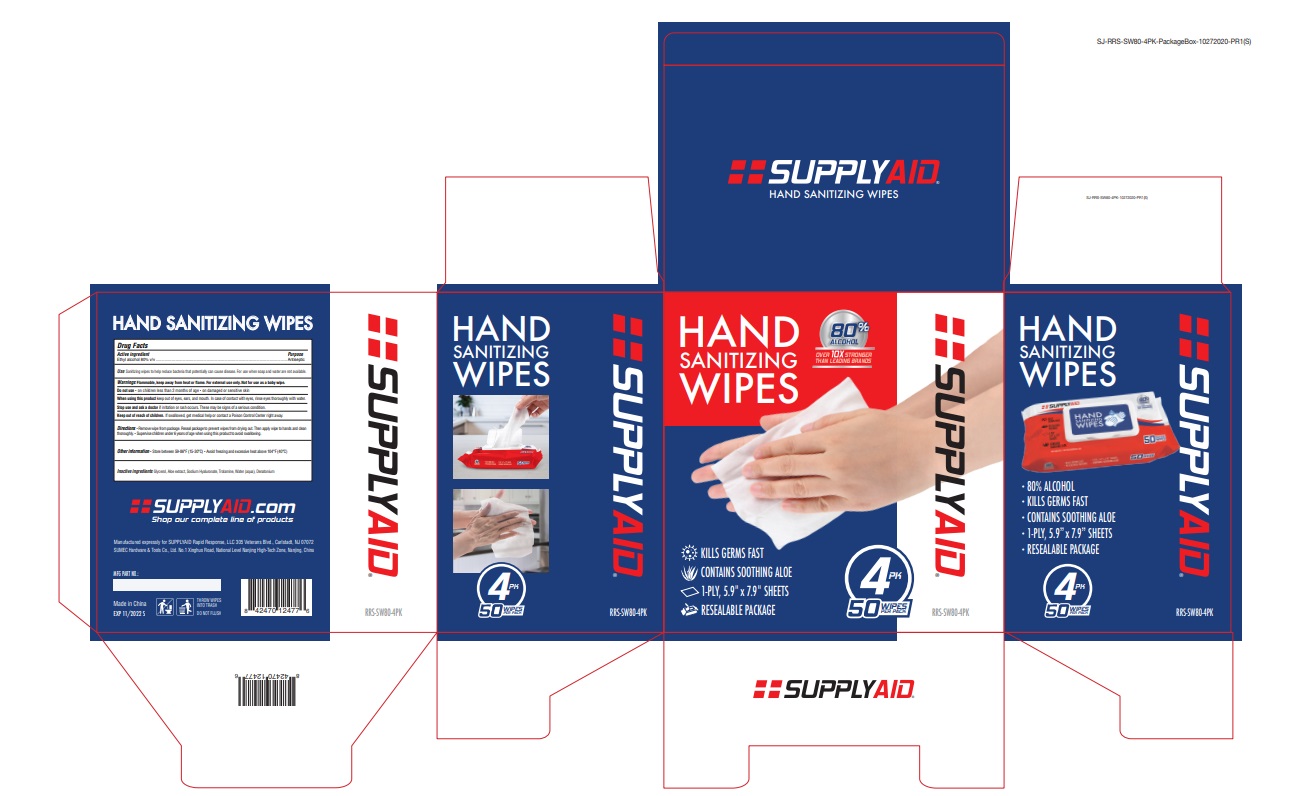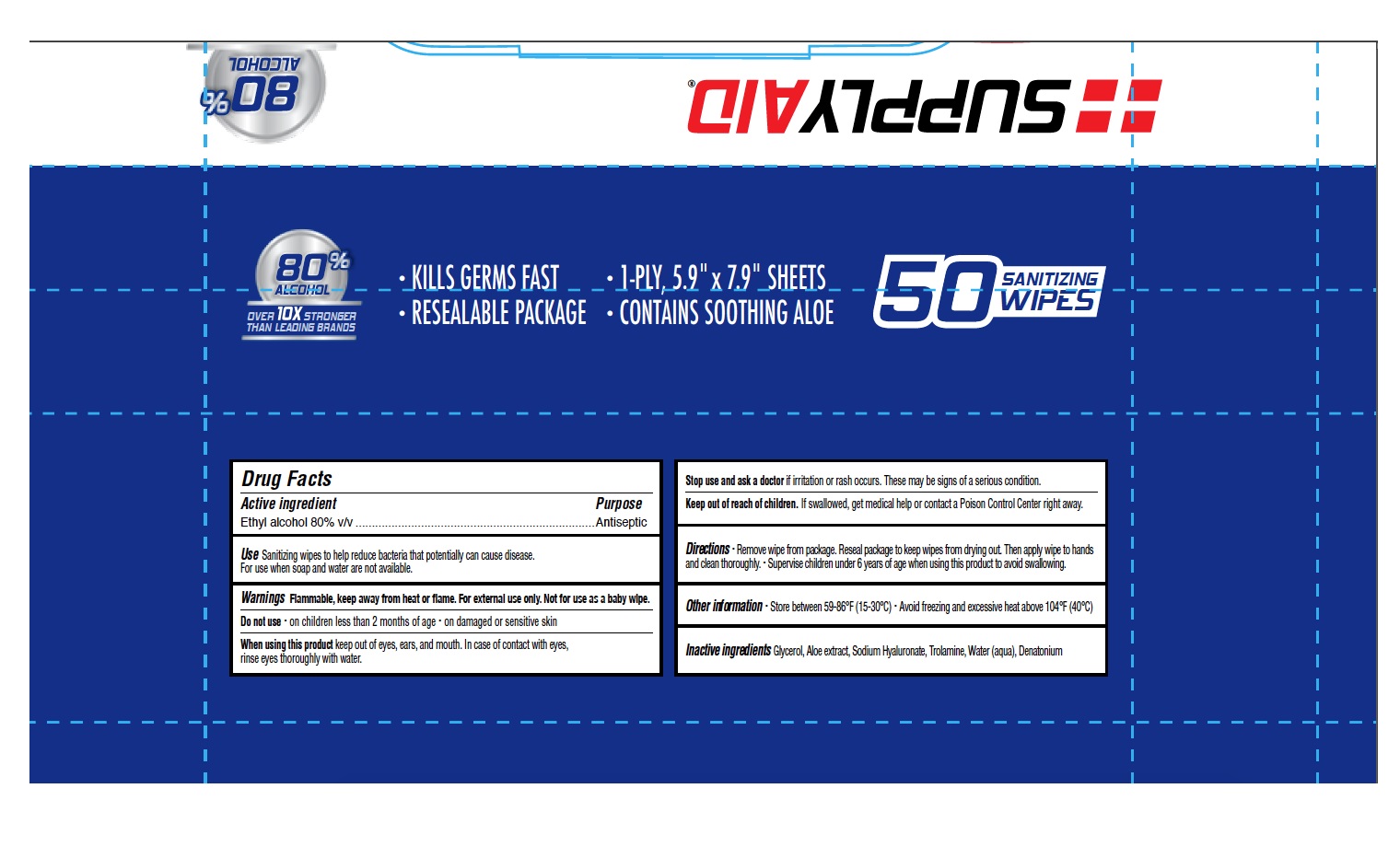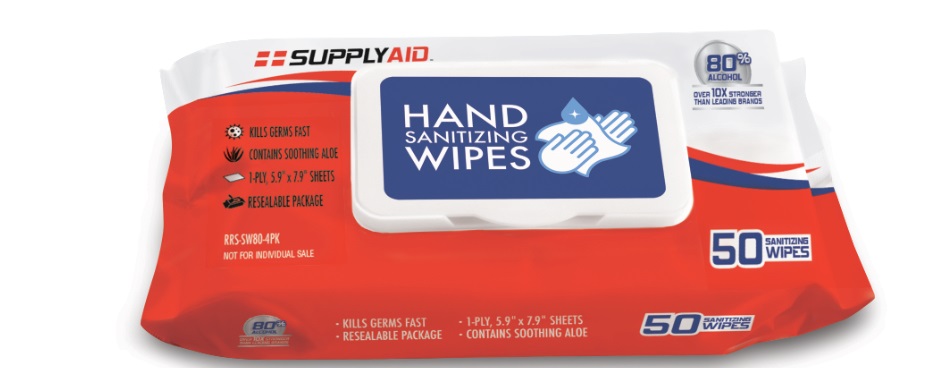 DRUG LABEL: Hand Sanitizer
NDC: 74251-205 | Form: CLOTH
Manufacturer: Supplyaid Rapid Response
Category: otc | Type: HUMAN OTC DRUG LABEL
Date: 20211123

ACTIVE INGREDIENTS: ALCOHOL 80 mL/100 mL
INACTIVE INGREDIENTS: WATER; ALOE; GLYCERIN; DENATONIUM; TROLAMINE

Product is hand sanitizing wipes

1. Alcohol (ethanol) (USP or Food Chemical Codex (FCC) grade) (80%, volume/volume (v/v)) in an aqueous solution denatured according to Alcohol and Tobacco Tax and Trade Bureau regulations in 27 CFR part 20.
2. Glycerol.
3. Sosium Hyaluronate.
4. Aloe extract
5. Trolamine
6. Water.
7. Denatorium

Active Ingredient(s)

Alcohol 80% v/v. Purpose: Antiseptic

Purpose

Antiseptic, Hand Sanitizer

Use

Sanitizing wipes er to help reduce bacteria that potentially can cause disease. For use when soap and water are not available.

Warnings

For external use only. Flammable. Keep away from heat or flame

Do not use

- on children less than 2 months of age
- on damaged or sensitive skin

When using this product keep out of eyes, ears, and mouth. In case of contact with eyes, rinse eyes thoroughly with water.
Stop use and ask a doctor if irritation or rash occurs. These may be signs of a serious condition.
Keep out of reach of children. If swallowed, get medical help or contact a Poison Control Center right away.

Stop use and ask a doctor if irritation or rash occurs. These may be signs of a serious condition.

Keep out of reach of children. If swallowed, get medical help or contact a Poison Control Center right away.

Directions

- Remove wipe from package. Reseal package to keep wipes from drying out. Then apply wipe to hands and clean thoroughly.
- Supervise children under 6 years of age when using this product to avoid swallowing.

Other information

- Store between 15-30C (59-86F)
- Avoid freezing and excessive heat above 40C (104F)

Inactive ingredients

glycerol, aloe extract, sodium hyaluronate, trolamine, wtaer, denatonium

Package Label - Principal Display Panel

NDC: 74251-205-11